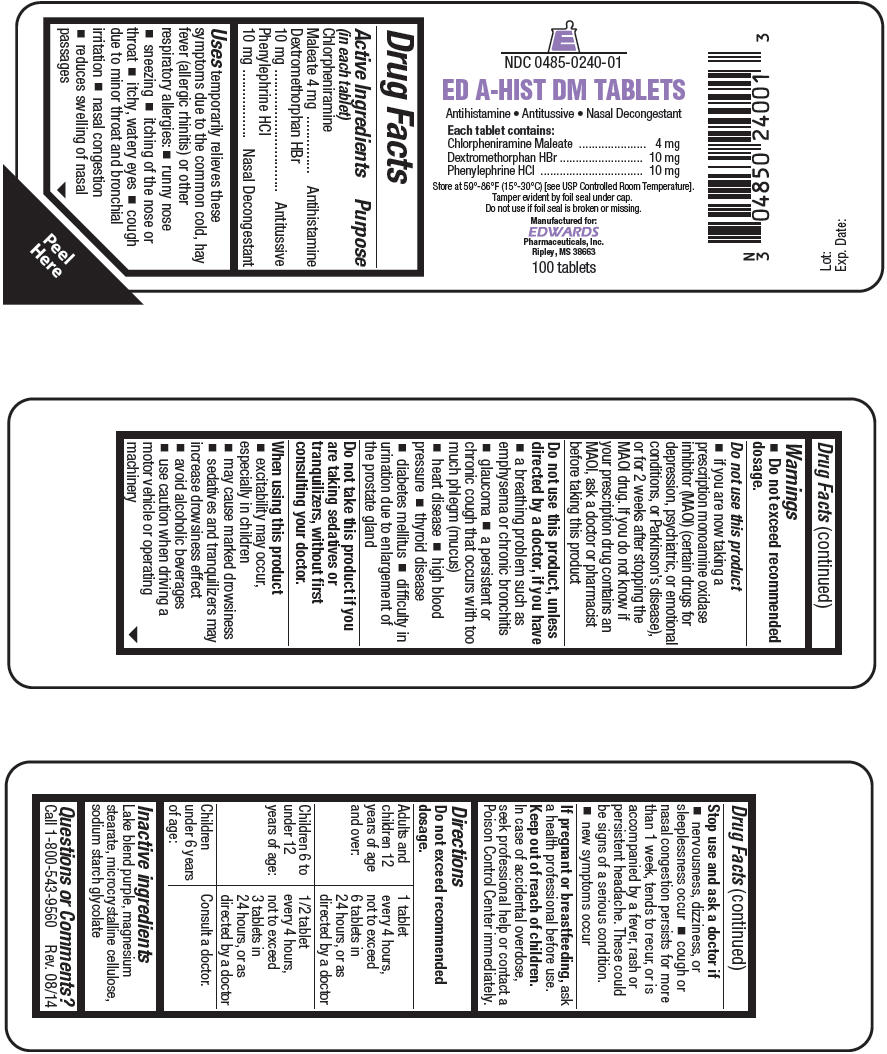 DRUG LABEL: ED-A-HIST DM
NDC: 0485-0240 | Form: TABLET, COATED
Manufacturer: EDWARDS PHARMACEUTICALS, INC.
Category: otc | Type: HUMAN OTC DRUG LABEL
Date: 20251106

ACTIVE INGREDIENTS: CHLORPHENIRAMINE MALEATE 4 mg/1 1; DEXTROMETHORPHAN HYDROBROMIDE 10 mg/1 1; PHENYLEPHRINE HYDROCHLORIDE 10 mg/1 1
INACTIVE INGREDIENTS: MAGNESIUM STEARATE; CELLULOSE, MICROCRYSTALLINE; SODIUM STARCH GLYCOLATE TYPE A CORN; FD&C RED NO. 40; FD&C BLUE NO. 2

ED-A-HIST DM TABLETS

Drug Facts

ACTIVE INGREDIENT

Active Ingredients (in each tablet) | Purpose
Chlorpheniramine Maleate 4 mg | Antihistamine
Dextromethorphan HBr 10 mg | Antitussive
Phenylephrine HCl 10 mg | Nasal Decongestant

Uses

temporarily relieves these symptoms due to the common cold, hay fever (allergic rhinitis) or other respiratory allergies:

- runny nose
- sneezing
- itching of the nose or throat
- itchy, watery eyes
- cough due to minor throat and bronchial irritation
- nasal congestion
- reduces swelling of nasal passages

Warnings

- Do not exceed recommended dosage.

Do not use this product

- if you are now taking a prescription monoamine oxidase inhibitor (MAOI) (certain drugs for depression, psychiatric, or emotional conditions, or Parkinson's disease), or for 2 weeks after stopping the MAOI drug. If you do not know if your prescription drug contains an MAOI, ask a doctor or pharmacist before taking this product

Do not use this product, unless directed by a doctor, if you have

- a breathing problem such as emphysema or chronic bronchitis
- glaucoma
- a persistent or chronic cough that occurs with too much phlegm (mucus)
- heart disease
- high blood pressure
- thyroid disease
- diabetes mellitus
- difficulty in urination due to enlargement of the prostate gland

ASK DOCTOR/PHARMACIST

Do not take this product if you are taking sedatives or tranquilizers, without first consulting your doctor.

When using this product

- excitability may occur, especially in children
- may cause marked drowsiness
- sedatives and tranquilizers may increase drowsiness effect
- avoid alcoholic beverages
- use caution when driving a motor vehicle or operating machinery

Stop use and ask a doctor if

- nervousness, dizziness, or sleeplessness occur
- cough or nasal congestion persists for more than 1 week, tends to recur, or is accompanied by a fever, rash or persistent headache. These could be signs of a serious condition.
- new symptoms occur

PREGNANCY OR BREAST FEEDING

If pregnant or breastfeeding, ask a health professional before use.

Keep out of reach of children. In case of accidental overdose, seek professional help or contact a Poison Control Center immediately.

Directions

Do not exceed recommended dosage.

Adults and children 12 years of age and over: | 1 tablet every 4 hours, not to exceed 6 tablets in 24 hours, or as directed by a doctor
Children 6 to under 12 years of age: | 1/2 tablet every 4 hours, not to exceed 3 tablets in 24 hours, or as directed by a doctor
Children under 6 years of age: | Consult a doctor.

Inactive ingredients

Lake blend purple, magnesium stearate, microcrystalline cellulose, sodium starch glycolate

Questions or Comments?

Call 1-800-543-9560 Rev. 08/14

PRINCIPAL DISPLAY PANEL - 100 Tablet Bottle Label

NDC 0485-0240-01

ED A-HIST DM TABLETS

Antihistamine • Antitussive • Nasal Decongestant

Each tablet contains:
Chlorpheniramine Maleate 4 mg
Dextromethorphan HBr 10 mg
Phenylephrine HCl 10 mg

Store at 59°-86°F (15°-30°C) [see USP Controlled Room Temperature].
Tamper evident by foil seal under cap.
Do not use if foil seal is broken or missing.

Manufactured for:
EDWARDS
Pharmaceuticals, Inc.
Ripley, MS 38663

100 tablets